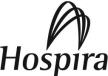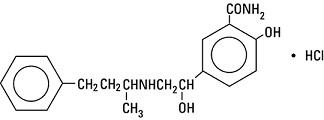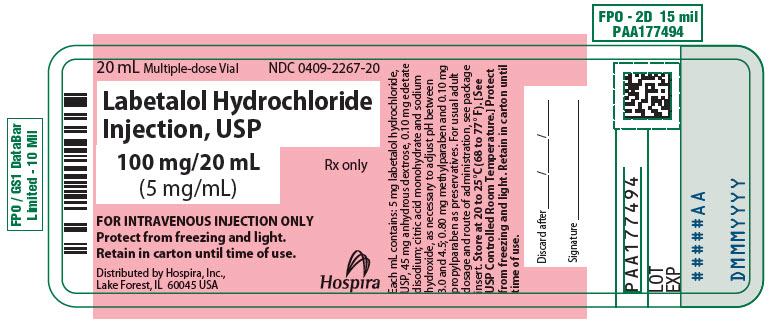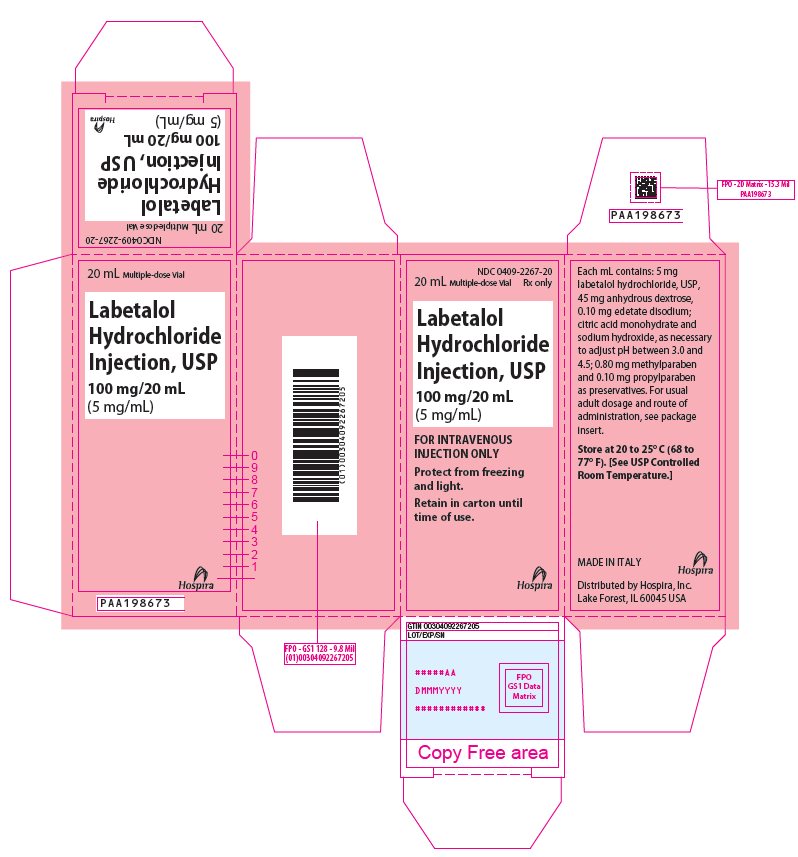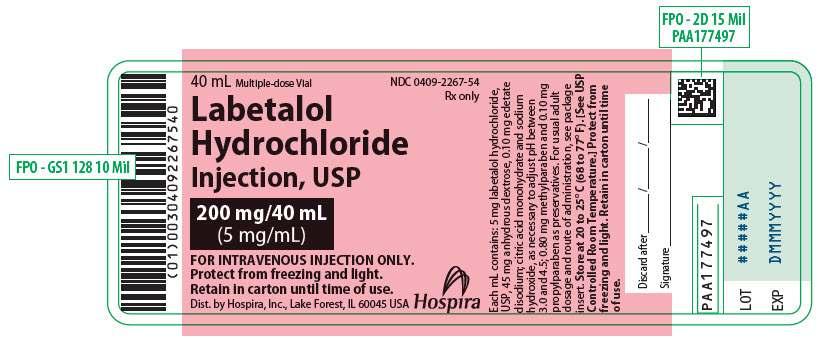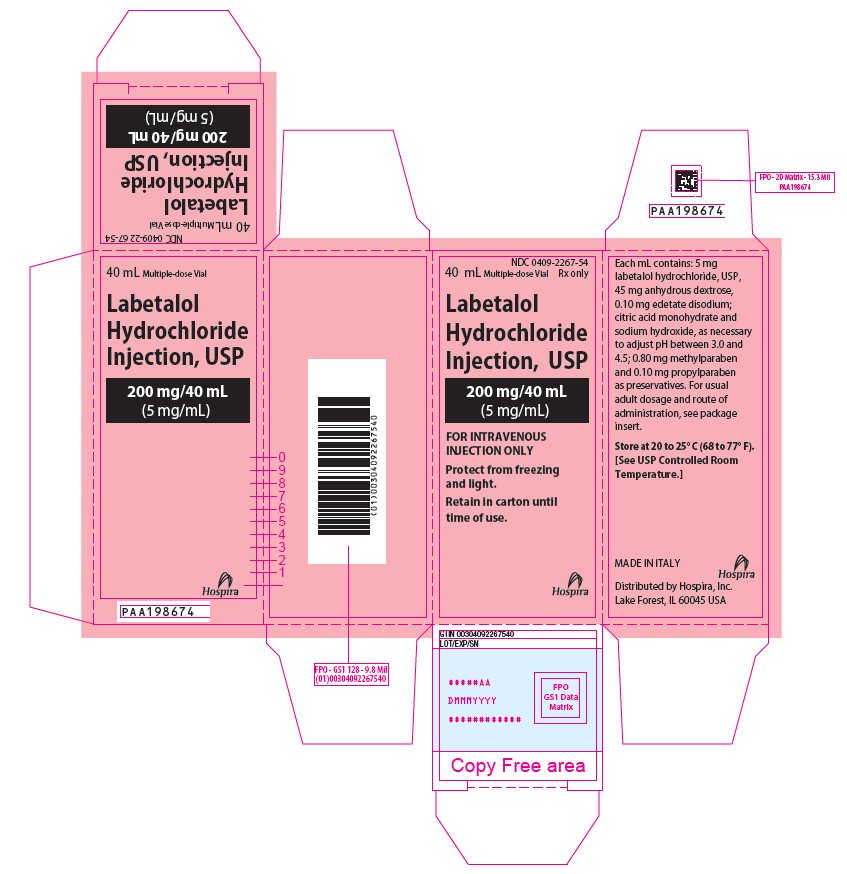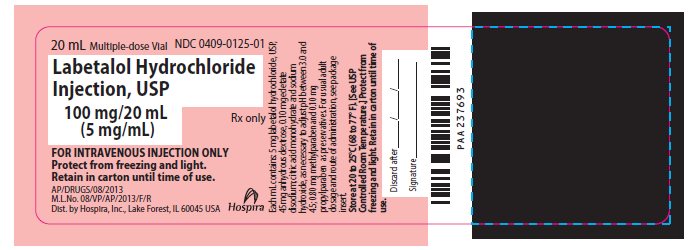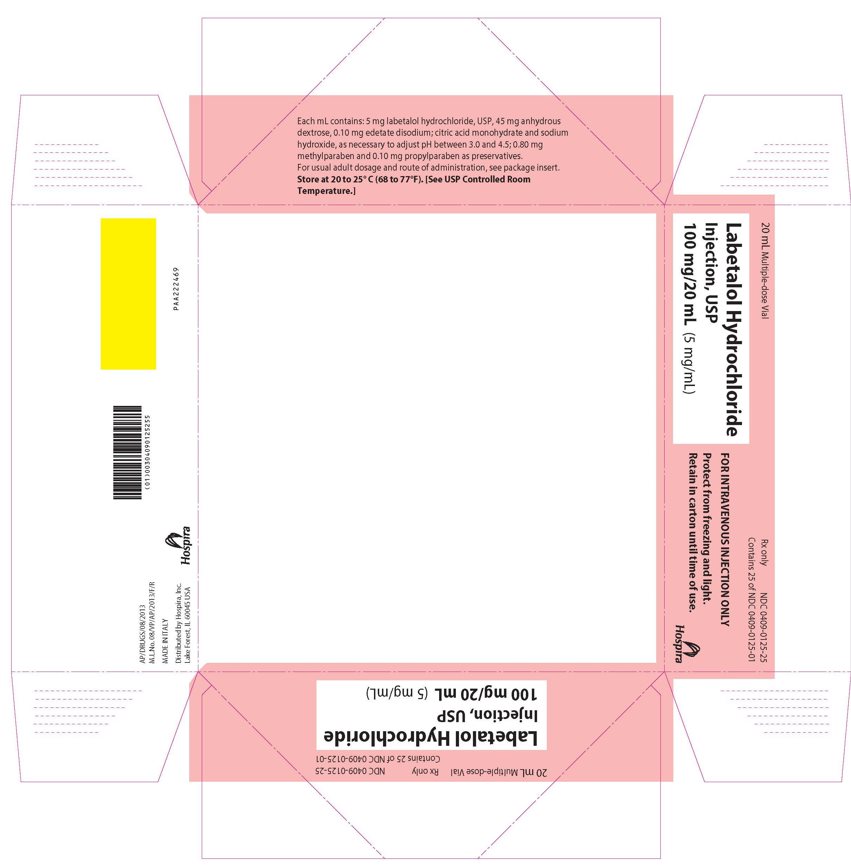 DRUG LABEL: Labetalol Hydrochloride
NDC: 0409-2267 | Form: INJECTION, SOLUTION
Manufacturer: Hospira, Inc.
Category: prescription | Type: HUMAN PRESCRIPTION DRUG LABEL
Date: 20251210

ACTIVE INGREDIENTS: LABETALOL HYDROCHLORIDE 5 mg/1 mL
INACTIVE INGREDIENTS: ANHYDROUS DEXTROSE 45 mg/1 mL; EDETATE DISODIUM 0.1 mg/1 mL; METHYLPARABEN 0.8 mg/1 mL; PROPYLPARABEN 0.1 mg/1 mL; CITRIC ACID MONOHYDRATE; SODIUM HYDROXIDE

Labetalol Hydrochloride

Injection, USP

Rx only

DESCRIPTION

Labetalol hydrochloride is an adrenergic receptor blocking agent that has both selective alpha1- and nonselective beta-adrenergic receptor blocking actions in a single substance.

Labetalol HCl is a racemate, chemically designated as 5-[1-hydroxy-2-[(1-methyl-3-phenylpropyl) amino] ethyl]-salicylamide monohydrochloride, and has the following structural formula:

Labetalol hydrochloride has the molecular formula C19H24N2O3 • HCl and a molecular weight of 364.87. It has two asymmetric centers and therefore exists as a molecular complex of two diastereoisomeric pairs. Dilevalol, the R,R' stereoisomer, makes up 25% of racemic labetalol.

Labetalol hydrochloride is a white or off-white crystalline powder, soluble in water.

Labetalol hydrochloride injection is a clear, colorless to light yellow aqueous sterile isotonic solution for intravenous injection. It has a pH range of 3.0 to 4.5. Each mL contains 5 mg labetalol hydrochloride, USP, 45 mg anhydrous dextrose, 0.1 mg edetate disodium; 0.8 mg methylparaben and 0.1 mg propylparaben as preservatives; citric acid monohydrate and sodium hydroxide, as necessary, to bring the solution into the pH range.

CLINICAL PHARMACOLOGY

Labetalol combines both selective, competitive alpha1-adrenergic blocking and nonselective, competitive beta-adrenergic blocking activity in a single substance. In man, the ratios of alpha- to beta-blockade have been estimated to be approximately 1:3 and 1:7 following oral and intravenous administration, respectively. Beta2-agonist activity has been demonstrated in animals with minimal beta1-agonist (ISA) activity detected. In animals, at doses greater than those required for alpha- or beta-adrenergic blockade, a membrane-stabilizing effect has been demonstrated.

Pharmacodynamics

The capacity of labetalol to block alpha-receptors in man has been demonstrated by attenuation of the presser effect of phenylephrine and by a significant reduction of the presser response caused by immersing the hand in ice-cold water ("cold-presser test"). Labetalol's beta1-receptor blockade in man was demonstrated by a small decrease in the resting heart rate, attenuation of tachycardia produced by isoproterenol or exercise, and by attenuation of the reflex tachycardia to the hypotension produced by amyl nitrite. Beta2-receptor blockade was demonstrated by inhibition of the isoproterenol-induced fall in diastolic blood pressure. Both the alpha- and beta-blocking actions of orally administered labetalol contribute to a decrease in blood pressure in hypertensive patients. Labetalol consistently, in dose-related fashion, blunted increases in exercise-induced blood pressure and heart rate, and in their double product. The pulmonary circulation during exercise was not affected by labetalol dosing.

Single oral doses of labetalol administered in patients with coronary artery disease had no significant effect on sinus rate, intraventricular conduction, or QRS duration. The atrioventricular (AV) conduction time was modestly prolonged in 2 of 7 patients. In another study, intravenous labetalol slightly prolonged AV nodal conduction time and atrial effective refractory period with only small changes in heart rate. The effects on AV nodal refractoriness were inconsistent.

Labetalol produces dose-related falls in blood pressure without reflex tachycardia and without significant reduction in heart rate, presumably through a mixture of its alpha-blocking and beta-blocking effects. Hemodynamic effects are variable with small nonsignificant changes in cardiac output seen in some studies but not others, and small decreases in total peripheral resistance. Elevated plasma renins are reduced.

Doses of labetalol that controlled hypertension did not affect renal function in mild to severe hypertensive patients with normal renal function.

Due to the alpha1-receptor blocking activity of labetalol, blood pressure is lowered more in the standing than in the supine position, and symptoms of postural hypotension can occur. During dosing with intravenous labetalol, the contribution of the postural component should be considered when positioning patients for treatment, and patients should not be allowed to move to an erect position unmonitored until their ability to do so is established.

In a clinical pharmacologic study in severe hypertensives, an initial 0.25 mg/kg injection of labetalol, administered to patients in the supine position, decreased blood pressure by an average of 11/7 mmHg. Additional injections of 0.5 mg/kg at 15 minute intervals up to a total cumulative dose of 1.75 mg/kg of labetalol caused further dose-related decreases in blood pressure. Some patients required cumulative doses of up to 3.25 mg/kg. The maximal effect of each dose level occurred within 5 minutes. Following discontinuation of intravenous treatment with labetalol, the blood pressure rose gradually and progressively approaching pretreatment baseline values within an average of 16 to 18 hours in the majority of patients.

Similar results were obtained in the treatment of patients with severe hypertension requiring urgent blood pressure reduction with an initial dose of 20 mg (which corresponds to 0.25 mg/kg for an 80 kg patient) followed by additional doses of either 40 or 80 mg at 10 minute intervals to achieve the desired effect or up to a cumulative dose of 300 mg.

Labetalol administered as a continuous intravenous infusion, with a mean dose of 136 mg (27 to 300 mg) over a period of 2 to 3 hours (mean of 2 hours and 39 minutes) lowered the blood pressure by an average of 60/35 mmHg.

Exacerbation of angina and, in some cases, myocardial infarction and ventricular dysrhythmias have been reported after abrupt discontinuation of therapy with beta-adrenergic blocking agents in patients with coronary artery disease. Abrupt withdrawal of these agents in patients without coronary artery disease has resulted in transient symptoms, including tremulousness, sweating, palpitation, headache and malaise. Several mechanisms have been proposed to explain these phenomena, among them increased sensitivity to catecholamines because of increased numbers of beta-receptors.

Although beta-adrenergic receptor blockade is useful in the treatment of angina and hypertension, there are also situations in which sympathetic stimulation is vital. For example, in patients with severely damaged hearts, adequate ventricular function may depend on sympathetic drive. Beta-adrenergic blockade may worsen AV block by preventing the necessary facilitating effects of sympathetic activity on conduction. Beta2-adrenergic blockade results in passive bronchial constriction by interfering with endogenous adrenergic bronchodilator activity in patients subject to bronchospasm and may also interfere with exogenous bronchodilators in such patients.

Pharmacokinetics and Metabolism

Following intravenous infusion, the elimination half-life is about 5.5 hours and the total body clearance is approximately 33 mL/min/kg. The plasma half-life of labetalol following oral administration is about 6 to 8 hours. In patients with decreased hepatic or renal function, the elimination half-life of labetalol is not altered; however, the relative bioavailability in hepatically impaired patients is increased due to decreased "first-pass" metabolism.

The metabolism of labetalol is mainly through conjugation to glucuronide metabolites. These metabolites are present in plasma and are excreted in the urine and, via the bile, into the feces. Approximately 55% to 60% of a dose appears in the urine as conjugates or unchanged labetalol within the first 24 hours of dosing.

Labetalol has been shown to cross the placental barrier in humans. Only negligible amounts of the drug crossed the blood-brain barrier in animal studies. Labetalol is approximately 50% protein bound. Neither hemodialysis nor peritoneal dialysis removes a significant amount of labetalol from the general circulation (<1%).

INDICATIONS AND USAGE

Labetalol HCl injection is indicated for control of blood pressure in severe hypertension.

CONTRAINDICATIONS

Labetalol HCl injection is contraindicated in bronchial asthma, overt cardiac failure, greater than first degree heart block, cardiogenic shock, severe bradycardia, other conditions associated with severe and prolonged hypotension, and in patients with a history of hypersensitivity to any component of the product (see WARNINGS).

Beta-blockers, even those with apparent cardioselectivity, should not be used in patients with a history of obstructive airway disease, including asthma.

WARNINGS

Hepatic Injury

Severe hepatocellular injury, confirmed by rechallenge in at least one case, occurs rarely with labetalol therapy. The hepatic injury is usually reversible, but hepatic necrosis and death have been reported. Injury has occurred after both short- and long-term treatment and may be slowly progressive despite minimal symptomatology. Similar hepatic events have been reported with a related compound, dilevalol HCl, including two deaths. Dilevalol HCl is one of the four isomers of labetalol. Thus, for patients taking labetalol, periodic determination of suitable hepatic laboratory tests would be appropriate. Laboratory testing should also be done at the very first symptom or sign of liver dysfunction (e.g., pruritus, dark urine, persistent anorexia, jaundice, right upper quadrant tenderness, or unexplained "flu-like" symptoms). If the patient has jaundice or laboratory evidence of liver injury, labetalol should be stopped and not restarted.

Cardiac Failure

Sympathetic stimulation is a vital component supporting circulatory function in congestive heart failure. Beta-blockade carries a potential hazard of further depressing myocardial contractility and precipitating more severe failure. Although beta-blockers should be avoided in overt congestive heart failure, if necessary, labetalol can be used with caution in patients with a history of heart failure, who are well compensated. Congestive heart failure has been observed in patients receiving labetalol. Labetalol does not abolish the inotropic action of digitalis on heart muscle.

In Patients without a History of Cardiac Failure

In patients with latent cardiac insufficiency, continued depression of the myocardium with beta-blocking agents over a period of time can lead, in some cases, to cardiac failure. At the first sign or symptom of impending cardiac failure, patients should be fully digitalized and/or be given a diuretic, and the response observed closely. If cardiac failure continues, despite adequate digitalization and diuretic, labetalol therapy should be withdrawn (gradually if possible).

Ischemic Heart Disease

Angina pectoris has not been reported upon labetalol discontinuation. However, following abrupt cessation of therapy with some beta-blocking agents in patients with coronary artery disease, exacerbations of angina pectoris and, in some cases, myocardial infarction have been reported. Therefore, such patients should be cautioned against interruption of therapy without the physician's advice. Even in the absence of overt angina pectoris, when discontinuation of labetalol is planned, the patient should be carefully observed and should be advised to limit physical activity. If angina markedly worsens or acute coronary insufficiency develops, labetalol administration should be reinstituted promptly, at least temporarily, and other measures appropriate for the management of unstable angina should be taken.

Nonallergic Bronchospasm (e.g., chronic bronchitis and emphysema)

Since labetalol injection at the usual intravenous therapeutic doses has not been studied in patients with nonallergic bronchospastic disease, it should not be used in such patients.

Pheochromocytoma

Intravenous labetalol has been shown to be effective in lowering the blood pressure and relieving symptoms in patients with pheochromocytoma; higher than usual doses may be required. However, paradoxical hypertensive responses have been reported in a few patients with this tumor; therefore, use caution when administering labetalol to patients with pheochromocytoma.

Diabetes Mellitus and Hypoglycemia

Beta-adrenergic blockade may prevent the appearance of premonitory signs and symptoms (e.g., tachycardia) of acute hypoglycemia. This is especially important with labile diabetics. Beta-blockade also reduces the release of insulin in response to hyperglycemia; it may therefore be necessary to adjust the dose of antidiabetic drugs.

Major Surgery

Do not routinely withdraw chronic beta blocker therapy prior to surgery. The effect of labetalol's alpha adrenergic activity has not been evaluated in this setting.

Several deaths have occurred when labetalol injection was used during surgery (including when used in cases to control bleeding).

A synergism between labetalol and halothane anesthesia has been shown (see PRECAUTIONS - Drug Interactions).

Rapid Decreases of Blood Pressure

Caution must be observed when reducing severely elevated blood pressure. A number of adverse reactions, including cerebral infarction, optic nerve infarction, angina, and ischemic changes in the electrocardiogram, have been reported with other agents when severely elevated blood pressure was reduced over time courses of several hours to as long as 1 or 2 days. The desired blood pressure lowering should therefore be achieved over as long a period of time as is compatible with the patient's status.

PRECAUTIONS

General

Impaired Hepatic Function

Labetalol injection should be used with caution in patients with impaired hepatic function since metabolism of the drug may be diminished.

Hypotension

Symptomatic postural hypotension (incidence 58%) is likely to occur if patients are tilted or allowed to assume the upright position within 3 hours of receiving labetalol injection. Therefore, the patient's ability to tolerate an upright position should be established before permitting any ambulation.

Intraoperative Floppy Iris Syndrome (IFIS) has been observed during cataract surgery in some patients treated with alpha-1 blockers (labetalol is an alpha/beta blocker). This variant of small pupil syndrome is characterized by the combination of a flaccid iris that billows in response to intraoperative irrigation currents, progressive intraoperative miosis despite preoperative dilation with standard mydriatic drugs, and potential prolapse of the iris toward the phacoemulsification incisions. The patient's ophthalmologist should be prepared for possible modifications to the surgical technique, such as the utilization of iris hooks, iris dilator rings, or viscoelastic substances. There does not appear to be a benefit of stopping alpha-1 blocker therapy prior to cataract surgery.

Following Coronary Artery Bypass Surgery

In one uncontrolled study, patients with low cardiac indices and elevated systemic vascular resistance following intravenous labetalol experienced significant declines in cardiac output with little change in systemic vascular resistance. One of these patients developed hypotension following labetalol treatment. Therefore, use of labetalol should be avoided in such patients.

High-Dose Labetalol

Administration of up to 3 g/d as an infusion for up to 2 to 3 days has been anecdotally reported; several patients experienced hypotension or bradycardia.

Jaundice or Hepatic Dysfunction

(See WARNINGS.)

Information for Patients

The following information is intended to aid in the safe and effective use of this medication. It is not a disclosure of all possible adverse or intended effects. During and immediately following (for up to 3 hours) labetalol injection, the patient should remain supine. Subsequently, the patient should be advised on how to proceed gradually to become ambulatory, and should be observed at the time of first ambulation.

When the patient is started on labetalol hydrochloride tablets following adequate control of blood pressure with labetalol hydrochloride injection, appropriate directions for titration of dosage should be provided (see DOSAGE AND ADMINISTRATION).

As with all drugs with beta-blocking activity, certain advice to patients being treated with labetalol is warranted: While no incident of the abrupt withdrawal phenomenon (exacerbation of angina pectoris) has been reported with labetalol, dosing with labetalol tablets should not be interrupted or discontinued without a physician's advice. Patients being treated with labetalol tablets should consult a physician at any signs or symptoms of impending cardiac failure or hepatic dysfunction (see WARNINGS). Also, transient scalp tingling may occur, usually when treatment with labetalol tablets is initiated (see ADVERSE REACTIONS).

Laboratory Tests

Routine laboratory tests are ordinarily not required before or after intravenous labetalol. In patients with concomitant illnesses, such as impaired renal function, appropriate tests should be done to monitor these conditions.

Drug Interactions

Since labetalol injection may be administered to patients already being treated with other medications, including other antihypertensive agents, careful monitoring of these patients is necessary to detect and treat promptly any undesired effect from concomitant administration.

In one survey, 2.3% of patients taking labetalol orally in combination with tricyclic antidepressants experienced tremor as compared to 0.7% reported to occur with labetalol alone. The contribution of each of the treatments to this adverse reaction is unknown but the possibility of a drug interaction cannot be excluded.

Drugs possessing beta-blocking properties can blunt the bronchodilator effect of beta-receptor agonist drugs in patients with bronchospasm; therefore, doses greater than the normal antiasthmatic dose of beta-agonist bronchodilator drugs may be required.

Cimetidine has been shown to increase the bioavailability of labetalol administered orally. Since this could be explained either by enhanced absorption or by an alteration of hepatic metabolism of labetalol, special care should be used in establishing the dose required for blood pressure control in such patients.

Synergism has been shown between halothane anesthesia and intravenously administered labetalol. During controlled hypotensive anesthesia using labetalol in association with halothane, high concentrations (3% or above) of halothane should not be used because the degree of hypotension will be increased and because of the possibility of a large reduction in cardiac output and an increase in central venous pressure. The anesthesiologist should be informed when a patient is receiving labetalol.

Labetalol blunts the reflex tachycardia produced by nitroglycerin without preventing its hypotensive effect. If labetalol is used with nitroglycerin in patients with angina pectoris, additional antihypertensive effects may occur.

Care should be taken if labetalol is used concomitantly with calcium antagonists of the verapamil type.

When drug products that are alkaline, such as furosemide, have been administered in combination with labetalol, a white precipitate has been noted. Therefore, these drugs should not be administered in the same infusion line.

Risk of Anaphylactic Reaction

While taking beta-blockers, patients with a history of severe anaphylactic reactions to a variety of allergens may be more reactive to repeated challenge, either accidental, diagnostic, or therapeutic. Such patients may be unresponsive to the usual doses of epinephrine used to treat allergic reaction.

Drug/Laboratory Test Interactions

The presence of labetalol metabolites in the urine may result in falsely elevated levels of urinary catecholamines, metanephrine, normetanephrine, and vanillylmandelic acid (VMA) when measured by fluorimetric or photometric methods. In screening patients suspected of having a pheochromocytoma and being treated with labetalol, a specific method, such as a high-performance liquid chromatographic assay with solid phase extraction (e.g., J Chromatogr. 385:241, 1987) should be employed in determining levels of catecholamines.

Labetalol has also been reported to produce a false-positive test for amphetamine when screening urine for the presence of drugs using the commercially available assay methods Toxi-Lab A® (thin-layer chromatographic assay) and Emit-d.a.u.® (radioenzymatic assay). When patients being treated with labetalol have a positive urine test for amphetamine using these techniques, confirmation should be made by using more specific methods, such as a gas chromatographic-mass spectrometer technique.

Carcinogenesis, Mutagenesis, Impairment of Fertility

Long-term oral dosing studies with labetalol for 18 months in mice and for 2 years in rats showed no evidence of carcinogenesis. Studies with labetalol, using dominant lethal assays in rats and mice, and exposing microorganisms according to modified Ames tests, showed no evidence of mutagenesis.

Pregnancy

Teratogenic Effects

Teratogenic studies have been performed with labetalol in rats and rabbits at oral doses up to approximately 6 and 4 times the maximum recommended human dose (MRHD), respectively. No reproducible evidence of fetal malformations was observed. Increased fetal resorptions were seen in both species at doses approximating the MRHD. A teratology study performed with labetalol in rabbits at intravenous doses up to 1.7 times the MRHD revealed no evidence of drug-related harm to the fetus. There are no adequate and well-controlled studies in pregnant women. Labetalol should be used during pregnancy only if the potential benefit justifies the potential risk to the fetus.

Nonteratogenic Effects

Hypotension, bradycardia, hypoglycemia, and respiratory depression have been reported in infants of mothers who were treated with labetalol for hypertension during pregnancy. Oral administration of labetalol to rats during late gestation through weaning at doses of 2 to 4 times the MRHD caused a decrease in neonatal survival.

Labor and Delivery

Labetalol given to pregnant women with hypertension did not appear to affect the usual course of labor and delivery.

Nursing Mothers

Small amounts of labetalol (approximately 0.004% of the maternal dose) are excreted in human milk. Caution should be exercised when labetalol injection is administered to a nursing woman.

Pediatric Use

Safety and effectiveness in children have not been established.

ADVERSE REACTIONS

Labetalol injection is usually well tolerated. Most adverse effects have been mild and transient and in controlled trials involving 92 patients did not require labetalol withdrawal. Symptomatic postural hypotension (incidence 58%) is likely to occur if patients are tilted or allowed to assume the upright position within 3 hours of receiving labetalol injection. Moderate hypotension occurred in 1 of 100 patients while supine. Increased sweating was noted in 4 of 100 patients, and flushing occurred in 1 of 100 patients.

The following also were reported with labetalol injection with the incidence per 100 patients as noted:

Cardiovascular System: Ventricular arrhythmia in 1.

Central and Peripheral Nervous Systems: Dizziness in 9; tingling of the scalp/skin 7; hypoesthesia (numbness) and vertigo, 1 each.

Gastrointestinal System: Nausea in 13; vomiting 4; dyspepsia and taste distortion, 1 each.

Metabolic Disorders: Transient increases in blood urea nitrogen and serum creatinine levels occurred in 8 of 100 patients; these were associated with drops in blood pressure, generally in patients with prior renal insufficiency.

Psychiatric Disorders: Somnolence/yawning in 3.

Respiratory System: Wheezing in 1.

Skin: Pruritus in 1.

The incidence of adverse reactions depends upon the dose of labetalol. The largest experience is with oral labetalol. Certain of the side effects increased with increasing oral dose as shown in the table below which depicts the entire U.S. therapeutic trials data base for adverse reactions that are clearly or possibly dose related.

Labetalol Daily Dose (mg) | 200 | 300 | 400 | 600 | 800 | 900 | 1200 | 1600 | 2400
Number of Patients | 522 | 181 | 606 | 608 | 503 | 117 | 411 | 242 | 175
Dizziness (%) | 2 | 3 | 3 | 3 | 5 | 1 | 9 | 13 | 16
Fatigue | 2 | 1 | 4 | 4 | 5 | 3 | 7 | 6 | 10
Nausea | <1 | 0 | 1 | 2 | 4 | 0 | 7 | 11 | 19
Vomiting | 0 | 0 | <1 | <1 | <1 | 0 | 1 | 2 | 3
Dyspepsia | 1 | 0 | 2 | 1 | 1 | 0 | 2 | 2 | 4
Paresthesias | 2 | 0 | 2 | 2 | 1 | 1 | 2 | 5 | 5
Nasal Stuffiness | 1 | 1 | 2 | 2 | 2 | 2 | 4 | 5 | 6
Ejaculation Failure | 0 | 2 | 1 | 2 | 3 | 0 | 4 | 3 | 5
Impotence | 1 | 1 | 1 | 1 | 2 | 4 | 3 | 4 | 3
Edema | 1 | 0 | 1 | 1 | 1 | 0 | 1 | 2 | 2

In addition, a number of other less common adverse events have been reported:

Cardiovascular: Hypotension, and rarely, syncope, bradycardia, heart block.

Liver and Biliary System: Hepatic necrosis, hepatitis, cholestatic jaundice, elevated liver function tests.

Hypersensitivity: Rare reports of hypersensitivity (e.g., rash, urticaria, pruritus, angioedema, dyspnea) and anaphylactoid reactions.

The oculomucocutaneous syndrome associated with the beta-blocker practolol has not been reported with labetalol during investigational use and extensive foreign marketing experience.

Clinical Laboratory Tests

Among patients dosed with labetalol tablets, there have been reversible increases of serum transaminases in 4% of patients tested, and more rarely, reversible increases in blood urea.

OVERDOSAGE

Overdosage with labetalol injection causes excessive hypotension that is posture sensitive, and sometimes, excessive bradycardia. Patients should be placed supine and their legs raised if necessary to improve the blood supply to the brain. If overdosage with labetalol follows oral ingestion, gastric lavage or pharmacologically induced emesis (using syrup of ipecac) may be useful for removal of the drug shortly after ingestion. The following additional measures should be employed if necessary: Excessive bradycardia-administer atropine or epinephrine. Cardiac failure-administer a digitalis glycoside and a diuretic. Dopamine or dobutamine may also be useful. Hypotension-administer vasopressors, e.g., norepinephrine. There is pharmacological evidence that norepinephrine may be the drug of choice. Bronchospasm-administer epinephrine and/or an aerosolized beta2-agonist. Seizures-administer diazepam.

In severe beta-blocker overdose resulting in hypotension and/or bradycardia, glucagon has been shown to be effective when administered in large doses (5 to 10 mg rapidly over 30 seconds, followed by continuous infusion of 5 mg/hr that can be reduced as the patient improves).

Neither hemodialysis nor peritoneal dialysis removes a significant amount of labetalol from the general circulation (<1%).

The oral LD50 value of labetalol in the mouse is approximately 600 mg/kg and in the rat is greater than 2 g/kg. The intravenous LD50 in these species is 50 to 60 mg/kg.

DOSAGE AND ADMINISTRATION

Labetalol hydrochloride injection is intended for intravenous use in hospitalized patients. DOSAGE MUST BE INDIVIDUALIZED depending upon the severity of hypertension and the response of the patient during dosing.

Patients should always be kept in a supine position during the period of intravenous drug administration. A substantial fall in blood pressure on standing should be expected in these patients. The patient's ability to tolerate an upright position should be established before permitting any ambulation, such as using toilet facilities.

Either of two methods of administration of labetalol hydrochloride injection may be used: a) repeated intravenous injections, b) slow continuous infusion.

Repeated Intravenous Injection

Initially, labetalol hydrochloride injection should be given in a dose of 20 mg labetalol HCl (which corresponds to 0.25 mg/kg for an 80 kg patient) by slow intravenous injection over a 2-minute period.

Immediately before the injection and at 5 and 10 minutes after injection, supine blood pressure should be measured to evaluate response. Additional injections of 40 mg or 80 mg can be given at 10 minute intervals until a desired supine blood pressure is achieved or a total of 300 mg labetalol HCl has been injected. The maximum effect usually occurs within 5 minutes of each injection.

Slow Continuous Infusion

Labetalol hydrochloride injection is prepared for continuous intravenous infusion by diluting the contents with commonly used intravenous fluids (see below). Examples of methods of preparing the infusion solution are:

The contents of either two 20 mL vials (40 mL), or one 40 mL vial, are added to 160 mL of a commonly used intravenous fluid such that the resultant 200 mL of solution contains 200 mg of labetalol hydrochloride, 1 mg/mL. The diluted solution should be administered at a rate of 2 mL/min to deliver 2 mg/min.

Alternatively, the contents of either two 20 mL vials (40 mL), or one 40 mL vial, of labetalol hydrochloride injection are added to 250 mL of a commonly used intravenous fluid. The resultant solution will contain 200 mg of labetalol hydrochloride, approximately 2 mg/3 mL. The diluted solution should be administered at a rate of 3 mL/min to deliver approximately 2 mg/min.

The rate of infusion of the diluted solution may be adjusted according to the blood pressure response, at the discretion of the physician. To facilitate a desired rate of infusion, the diluted solution can be infused using a controlled administration mechanism, e.g., graduated burette or mechanically driven infusion pump.

Since the half-life of labetalol is 5 to 8 hours, steady-state blood levels (in the face of a constant rate of infusion) would not be reached during the usual infusion time period. The infusion should be continued until a satisfactory response is obtained and should then be stopped and oral labetalol hydrochloride started. The effective intravenous dose is usually in the range of 50 to 200 mg. A total dose of up to 300 mg may be required in some patients.

Blood Pressure Monitoring

The blood pressure should be monitored during and after completion of the infusion or intravenous injections. Rapid or excessive falls in either systolic or diastolic blood pressure during intravenous treatment should be avoided. In patients with excessive systolic hypertension, the decrease in systolic pressure should be used as indicator of effectiveness in addition to the response of the diastolic pressure.

Initiation of Dosing with Labetalol Hydrochloride Tablets

Subsequent oral dosing with labetalol hydrochloride tablets should begin when it has been established that the supine diastolic blood pressure has begun to rise. The recommended initial dose is 200 mg, followed in 6 to 12 hours by an additional dose of 200 or 400 mg, depending on the blood pressure response. Thereafter, inpatient titration with labetalol hydrochloride tablets may proceed as follows:

Inpatient Titration Instructions
Regimen | Daily Dose [If needed, the total daily dose may be given in three divided doses.]
200 mg b.i.d. | 400 mg
400 mg b.i.d. | 800 mg
800 mg b.i.d. | 1600 mg
1200 mg b.i.d. | 2400 mg

While in the hospital, the dosage of labetalol hydrochloride tablets may be increased at 1 day intervals to achieve the desired blood pressure reduction.

For subsequent outpatient titration or maintenance dosing see Labetalol Hydrochloride Tablets Product Information DOSAGE AND ADMINISTRATION for additional recommendations.

Compatibility with commonly used intravenous fluids

Parenteral drug products should be inspected visually for particulate matter and discoloration prior to administration, whenever solution and container permit.

Labetalol hydrochloride injection was tested for compatibility with commonly used intravenous fluids at final concentrations of 1.25 mg to 3.75 mg labetalol hydrochloride per mL of the mixture. Labetalol hydrochloride injection was found to be compatible with and stable (for 24 hours refrigerated or at room temperature) in mixtures with the following solutions:

Ringers Injection, USP

Lactated Ringers Injection, USP

5% Dextrose and Ringers Injection

5% Lactated Ringers and 5% Dextrose Injection

5% Dextrose Injection, USP

0.9% Sodium Chloride Injection, USP

5% Dextrose and 0.2% Sodium Chloride Injection, USP

2.5% Dextrose and 0.45% Sodium Chloride Injection, USP

5% Dextrose and 0.9% Sodium Chloride Injection, USP

5% Dextrose and 0.33% Sodium Chloride Injection, USP

Labetalol hydrochloride injection was NOT compatible with 5% Sodium Bicarbonate Injection, USP. Care should be taken when administering alkaline drugs, including furosemide, in combination with labetalol. Compatibility should be assured prior to administering these drugs together.

HOW SUPPLIED

Labetalol hydrochloride injection, USP 5 mg/mL, is supplied in:

Unit of Sale | Concentration
NDC 0409-2267-20 Carton containing 1 Multiple-dose Vial | 100 mg/20 mL (5 mg/mL)
NDC 0409-2267-54 Carton containing 1 Multiple-dose Vial | 200 mg/40 mL (5 mg/mL)
NDC 0409-0125-25; Tray containing 25; Multiple-dose Vials | 100 mg/20 mL; (5 mg/mL)

Store at 20 to 25°C (68 to 77°F). [See USP Controlled Room Temperature.] Protect from freezing and light.

Distributed by Hospira, Inc., Lake Forest, IL 60045 USA

LAB-1224-4.0

Revised: 11/2022

PRINCIPAL DISPLAY PANEL - 100 mg/20 mL Vial Label

20 mL Multiple-dose Vial
NDC 0409-2267-20

Labetalol Hydrochloride
Injection, USP

100 mg/20 mL
(5 mg/mL)

Rx only

FOR INTRAVENOUS INJECTION ONLY
Protect from freezing and light.
Retain in carton until time of use.

Distributed by Hospira, Inc.,
Lake Forest, IL 60045 USA

Hospira

PRINCIPAL DISPLAY PANEL - 100 mg/20 mL Vial Carton

NDC 0409-2267-20
20 mL Multiple-dose Vial
Rx only

Labetalol
Hydrochloride
Injection, USP
100 mg/20 mL
(5 mg/mL)

FOR INTRAVENOUS
INJECTION ONLY

Protect from freezing
and light.

Retain in carton until
time of use.

Hospira

PRINCIPAL DISPLAY PANEL - 200 mg/40 mL Vial Label

40 mL Multiple-dose Vial
NDC 0409-2267-54
Rx only

Labetalol
Hydrochloride
Injection, USP

200 mg/40 mL
(5 mg/mL)

FOR INTRAVENOUS INJECTION ONLY.
Protect from freezing and light.
Retain in carton until time of use.

Dist. by Hospira, Inc., Lake Forest, IL 60045 USA

Hospira

PRINCIPAL DISPLAY PANEL - 200 mg/40 mL Vial Carton

NDC 0409-2267-54
40 mL Multiple-dose Vial
Rx only

Labetalol
Hydrochloride
Injection, USP

200 mg/40 mL
(5 mg/mL)

FOR INTRAVENOUS
INJECTION ONLY

Protect from freezing
and light.

Retain in carton until
time of use.

Hospira

PRINCIPAL DISPLAY PANEL - 100 mg/20 mL Vial Label 0409-0125

20 mL Multiple-dose Vial
NDC 0409-0125-01

Labetalol Hydrochloride
Injection, USP

100 mg/20 mL
(5 mg/mL)

Rx only

FOR INTRAVENOUS INJECTION ONLY
Protect from freezing and light.
Retain in carton until time of use.

AP/DRUGS/08/2013
M.L.No. 08/VP/AP/2013/F/R
Dist. by Hospira, Inc., Lake Forest, IL 60045 USA

Hospira

PRINCIPAL DISPLAY PANEL - 100 mg/20 mL Vial Tray 0409-0125

20 mL Multiple-dose Vial
Rx only

NDC 0409-0125-25
Contains 25 of NDC 0409-0125-01

Labetalol Hydrochloride
Injection, USP
100 mg/20 mL (5 mg/mL)

FOR INTRAVENOUS INJECTION ONLY

Protect from freezing and light.
Retain in carton until time of use.

Hospira